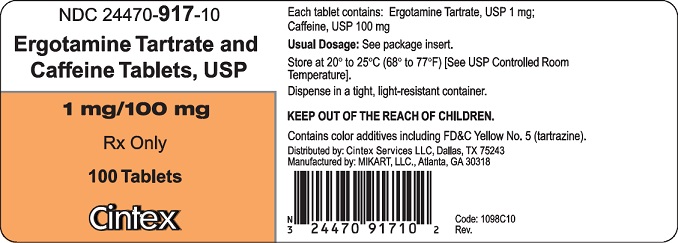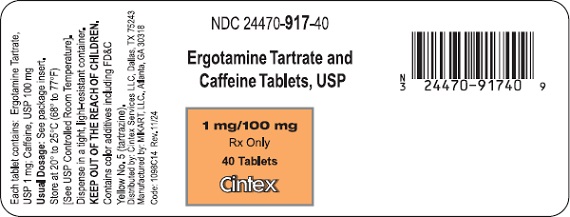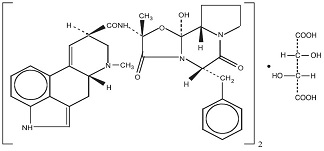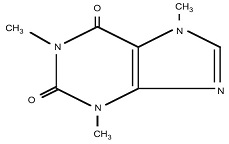 DRUG LABEL: ergotamine tartrate and caffeine
NDC: 24470-917 | Form: TABLET, FILM COATED
Manufacturer: Cintex Services, LLC
Category: prescription | Type: HUMAN PRESCRIPTION DRUG LABEL
Date: 20250327

ACTIVE INGREDIENTS: ERGOTAMINE TARTRATE 1 mg/1 1; CAFFEINE 100 mg/1 1
INACTIVE INGREDIENTS: CELLULOSE, MICROCRYSTALLINE; CROSPOVIDONE; FD&C BLUE NO. 2; FD&C RED NO. 40; FD&C YELLOW NO. 5; MAGNESIUM STEARATE; POLYETHYLENE GLYCOL, UNSPECIFIED; POLYVINYL ALCOHOL; SILICON DIOXIDE; TALC; TITANIUM DIOXIDE; WATER

Ergotamine Tartrate and Caffeine Tablets, USP 1 mg/100 mg

WARNING

Serious and/or life-threatening peripheral ischemia has been associated with the coadministration of ergotamine tartrate and caffeine tablets with potent CYP 3A4 inhibitors including protease inhibitors and macrolide antibiotics. Because CYP 3A4 inhibition elevates the serum levels of ergotamine tartrate and caffeine tablets, the risk for vasospasm leading to cerebral ischemia and/or ischemia of the extremities is increased. Hence, concomitant use of these medications is contraindicated (see also CONTRAINDICATIONS and WARNINGS sections).

DESCRIPTION

Each tablet for oral administration contains 1 mg ergotamine tartrate, USP, and 100 mg caffeine, USP.

ERGOTAMINE TARTRATE:

(C33H35N5O5)2• C4H6O6

M.W. 1313.41

Ergotaman-3’,6’,18-trione, 12’-hydroxy-2’-methyl-5’-(phenyl-methyl)-, (5’α), [R-(R*, R*)]-2,3-dihydroxy-butanedioate (2:1) (salt)

CAFFEINE:

C8H10N4O2 (anhydrous)

M.W. 194.19

1 H-Purine-2,6-dione, 3,7-dihydro-1,3,7-trimethyl-

Inactive ingredients include colloidal silicon dioxide, crospovidone, magnesium stearate, and microcrystalline cellulose. Film coating includes the following ingredients: macrogol/PEG 3350, polyvinyl alcohol, purified water, talc, titanium dioxide, FD&C blue #2 aluminum lake, FD&C red #40 aluminum lake, and FD&C yellow #5 tartrazine aluminum lake.

CLINICAL PHARMACOLOGY

Ergotamine is an alpha adrenergic blocking agent with a direct stimulating effect on the smooth muscle of peripheral and cranial blood vessels and produces depression of central vasomotor centers. The compound also has the properties of serotonin antagonism. In comparison to hydrogenated ergotamine, the adrenergic blocking actions are less pronounced and vasoconstrictive actions are greater.

Caffeine, also a cranial vasoconstrictor, is added to further enhance the vasoconstrictive effect without the necessity of increasing ergotamine dosage.

Many migraine patients experience excessive nausea and vomiting during attacks, making it impossible for them to retain any oral medication. In such cases, therefore, the only practical means of medication is through the rectal route where medication may reach the cranial vessels directly, evading the splanchnic vasculature and the liver.

Pharmacokinetics

Interactions: Pharmacokinetic interactions (increased blood levels of ergotamine) have been reported in patients treated orally with ergotamine and macrolide antibiotics (e.g., troleandomycin, clarithromycin, erythromycin), and in patients treated orally with ergotamine and protease inhibitors (e.g. ritonavir) presumably due to inhibition of cytochrome P450 3A metabolism of ergotamine (see CONTRAINDICATIONS). Ergotamine has also been shown to be an inhibitor of cytochrome P450 3A catalyzed reactions. No pharmacokinetic interactions involving other cytochrome P450 isoenzymes are known.

INDICATIONS AND USAGE

Ergotamine tartrate and caffeine tablets are indicated as therapy to abort or prevent vascular headache; e.g., migraine, migraine variants or so-called “histaminic cephalalgia.”

CONTRAINDICATIONS

Coadministration of ergotamine with potent CYP 3A4 inhibitors (ritonavir, nelfinavir, indinavir, erythromycin, clarithromycin, and troleandomycin) has been associated with acute ergot toxicity (ergotism) characterized by vasospasm and ischemia of the extremities (see PRECAUTIONS: Drug Interactions), with some cases resulting in amputation. There have been rare reports of cerebral ischemia in patients on protease inhibitor therapy when ergotamine tartrate and caffeine tablets was coadministered, at least one resulting in death. Because of the increased risk of ergotism and other serious vasospastic adverse events, ergotamine use is contraindicated with these drugs and other potent inhibitors of CYP 3A4 (e.g., ketoconazole, itraconazole) (see WARNINGS: CYP 3A4 Inhibitors).

Ergotamine tartrate and caffeine tablets may cause fetal harm when administered to pregnant women. Ergotamine tartrate and caffeine tablets is contraindicated in women who are or may become pregnant. If this drug is used during pregnancy or if the patient becomes pregnant while taking this product, the patient should be apprised of the potential hazard to the fetus.

Peripheral vascular disease, coronary heart disease, hypertension, impaired hepatic or renal function and sepsis.

Hypersensitivity to any of the components.

WARNINGS

CYP 3A4 Inhibitors (e.g. Macrolide Antibiotics and Protease Inhibitors)

Coadministration of ergotamine with potent CYP 3A4 inhibitors such as protease inhibitors or macrolide antibiotics has been associated with serious adverse events; for this reason, these drugs should not be given concomitantly with ergotamine (See CONTRAINDICATIONS). While these reactions have not been reported with less potent CYP 3A4 inhibitors, there is a potential risk for serious toxicity including vasospasm when these drugs are used with ergotamine. Examples of less potent CYP 3A4 inhibitors include: saquinavir, nefazodone, fluconazole, fluoxetine, grapefruit juice, fluvoxamine, zileuton, metronidazole, and clotrimazole. These lists are not exhaustive, and the prescriber should consider the effects on CYP 3A4 of other agents being considered for concomitant use with ergotamine.

Fibrotic Complications

There have been a few reports of patients on ergotamine tartrate and caffeine therapy developing retroperitoneal and/or pleuropulmonary fibrosis. There have also been rare reports of fibrotic thickening of the aortic, mitral, tricuspid, and/or pulmonary valves with long-term continuous use of ergotamine tartrate and caffeine. Ergotamine tartrate and caffeine tablets should not be used for chronic daily administration (see DOSAGE AND ADMINISTRATION).

PRECAUTIONS

This product contains FD&C Yellow No. 5 (tartrazine) which may cause allergic-type reactions (including bronchial asthma) in certain susceptible persons. Although the overall incidence of FD&C Yellow No. 5 (tartrazine) sensitivity in the general population is low, it is frequently seen in patients who also have aspirin hypersensitivity.

General

Although signs and symptoms of ergotism rarely develop even after long-term intermittent use of the orally administered drug, care should be exercised to remain within the limits of recommended dosage.

Ergotism is manifested by intense arterial vasoconstriction, producing signs and symptoms of peripheral vascular ischemia. Ergotamine induces vasoconstriction by a direct action on vascular smooth muscle. In chronic intoxication with ergot derivatives, headache, intermittent claudication, muscle pains, numbness, coldness, and pallor of the digits may occur. If the condition is allowed to progress untreated, gangrene can result.

While most cases of ergotism associated with ergotamine treatment result from frank overdosage, some cases have involved apparent hypersensitivity. There are few reports of ergotism among patients taking doses within the recommended limits or for brief periods of time. In rare instances, patients, particularly those who have used the medication indiscriminately over long periods of time, may display withdrawal symptoms consisting of rebound headache upon discontinuation of the drug.

Information for Patients

Patients should be advised that two tablets of ergotamine tartrate and caffeine tablets should be taken at the first sign of a migraine headache. No more than 6 tablets should be taken for any single migraine attack. No more than 10 tablets should be taken during any 7-day period. Administration of ergotamine tartrate and caffeine tablets should not exceed the dosing guidelines and should not be used for chronic daily administration (see DOSAGE AND ADMINISTRATION). Ergotamine tartrate and caffeine tablets should be used only for migraine headaches. It is not effective for other types of headaches and it lacks analgesic properties. Patients should be advised to report to the physician immediately any of the following: numbness or tingling in the fingers and toes, muscle pain in the arms and legs, weakness in the legs, pain in the chest or temporary speeding or slowing of the heart rate, swelling or itching.

Drug Interactions

CYP 3A4 Inhibitors (e.g. Macrolide Antibiotics and Protease Inhibitors)

See CONTRAINDICATIONS and WARNINGS.

Ergotamine tartrate and caffeine tablets should not be administered with other vasoconstrictors. Use with sympathomimetics (pressor agents) may cause extreme elevation of blood pressure. The beta-blocker Inderal (propranolol) has been reported to potentiate the vasoconstrictive action of ergotamine tartrate and caffeine tablets by blocking the vasodilating property of epinephrine. Nicotine may provoke vasoconstriction in some patients, predisposing to a greater ischemic response to ergot therapy.

The blood levels of ergotamine-containing drugs are reported to be elevated by the concomitant administration of macrolide antibiotics and vasospastic reactions have been reported with therapeutic doses of the ergotamine-containing drugs when coadministered with these antibiotics.

Pregnancy

Teratogenic Effects

Pregnancy Category X

There are no studies on the placental transfer or teratogenicity of the combined products of ergotamine tartrate and caffeine tablets. Caffeine is known to cross the placenta and has been shown to be teratogenic in animals. Ergotamine crosses the placenta in small amounts, although it does not appear to be embryotoxic in this quantity. However, prolonged vasoconstriction of the uterine vessels and/or increased myometrial tone leading to reduced myometrial and placental blood flow may have contributed to fetal growth retardation observed in animals (see CONTRAINDICATIONS).

Nonteratogenic Effects

Ergotamine tartrate and caffeine tablets is contraindicated in pregnancy due to the oxytocic effects of ergotamine (see CONTRAINDICATIONS).

Labor and Delivery

Ergotamine tartrate and caffeine tablets is contraindicated in labor and delivery due to its oxytocic effect which is maximal in the third trimester (see CONTRAINDICATIONS)

Nursing Mothers

Ergot drugs are known to inhibit prolactin but there are no reports of decreased lactation with ergotamine tartrate and caffeine. Ergotamine is excreted in breast milk and may cause symptoms of vomiting, diarrhea, weak pulse and unstable blood pressure in nursing infants. Because of the potential for serious adverse reactions in nursing infants from ergotamine tartrate and caffeine tablets, a decision should be made whether to discontinue nursing or discontinue the drug, taking into account the importance of the drug to the mother.

Pediatric Use

Safety and effectiveness in pediatric patients have not been established.

ADVERSE REACTIONS

Cardiovascular: Vasoconstrictive complications of a serious nature may occur at times. These include ischemia, cyanosis, absence of pulse, cold extremities, gangrene, precordial distress and pain, EKG changes and muscle pains. Although these effects occur most commonly with long-term therapy at relatively high doses, they have also been reported with short-term or normal doses. Other cardiovascular adverse effects include transient tachycardia or bradycardia and hypertension.

Gastrointestinal: Nausea and vomiting

Neurological: Paresthesias, numbness, weakness, and vertigo

Allergic: Localized edema and itching.

Fibrotic Complications: (see WARNINGS).

To report SUSPECTED ADVERSE REACTIONS, call 1-855-899-4237, or contact FDA at 1-800-FDA-1088 or www.fda.gov/medwatch.

DRUG ABUSE AND DEPENDENCE

There have been reports of drug abuse and psychological dependence in patients on ergotamine tartrate and caffeine tablets therapy. Due to the chronicity of vascular headaches, it is imperative that patients be advised not to exceed recommended dosages with long-term use to avoid ergotism (see PRECAUTIONS).

OVERDOSAGE

The toxic effects of an acute overdosage of ergotamine tartrate and caffeine tablets are due primarily to the ergotamine component. The amount of caffeine is such that its toxic effects will be overshadowed by those of ergotamine. Symptoms include vomiting; numbness, tingling, pain and cyanosis of the extremities associated with diminished or absent peripheral pulses; hypertension or hypotension; drowsiness, stupor, coma, convulsions and shock. A case has been reported of reversible bilateral papillitis with ring scotomata in a patient who received five times the recommended daily adult dose over a period of 14 days.

Treatment consists of removal of the offending drug by induction of emesis, gastric lavage, and catharsis. Maintenance of adequate pulmonary ventilation, correction of hypotension, and control of convulsions and blood pressure are important considerations. Treatment of peripheral vasospasm should consist of warmth, but not heat, and protection of the ischemic limbs. Vasodilators may be beneficial but caution must be exercised to avoid aggravating an already existent hypotension.

DOSAGE AND ADMINISTRATION

Procedure: For the best results, dosage should start at the first sign of an attack. Adults: Take 2 tablets at the start of attack; 1 additional tablet every ½ hour, if needed for full relief (maximum 6 tablets per attack, 10 per week).

Maximum Adult Dosage:

Total daily dose for any one attack should not exceed 6 tablets. Total weekly dosage should not exceed 10 tablets. Ergotamine tartrate and caffeine tablets should not be used for chronic daily administration. In carefully selected patients, with due consideration of maximum dosage recommendations, administration of the drug at bedtime may be an appropriate short-term preventive measure.

HOW SUPPLIED

Ergotamine tartrate and caffeine tablets, USP for oral administration are available as:

1 mg/100 mg: beige (film coated), round, convex face tablets, debossed “123” on one side and “MH” on the other side.

Bottles of 100......NDC 24470-917-10

Bottles of 40 .......NDC 24470-917-40

Store at 20° to 25°C (68° to 77°F) (see USP Controlled Room Temperature).

Dispense in a tight, light-resistant container.

KEEP OUT OF THE REACH OF CHILDREN.

Distributed by

Cintex Services, LLC

Dallas, TX 75243

Manufactured by

MIKART, LLC

Atlanta, GA 30318

Code 1098C00

Rev. 11/24